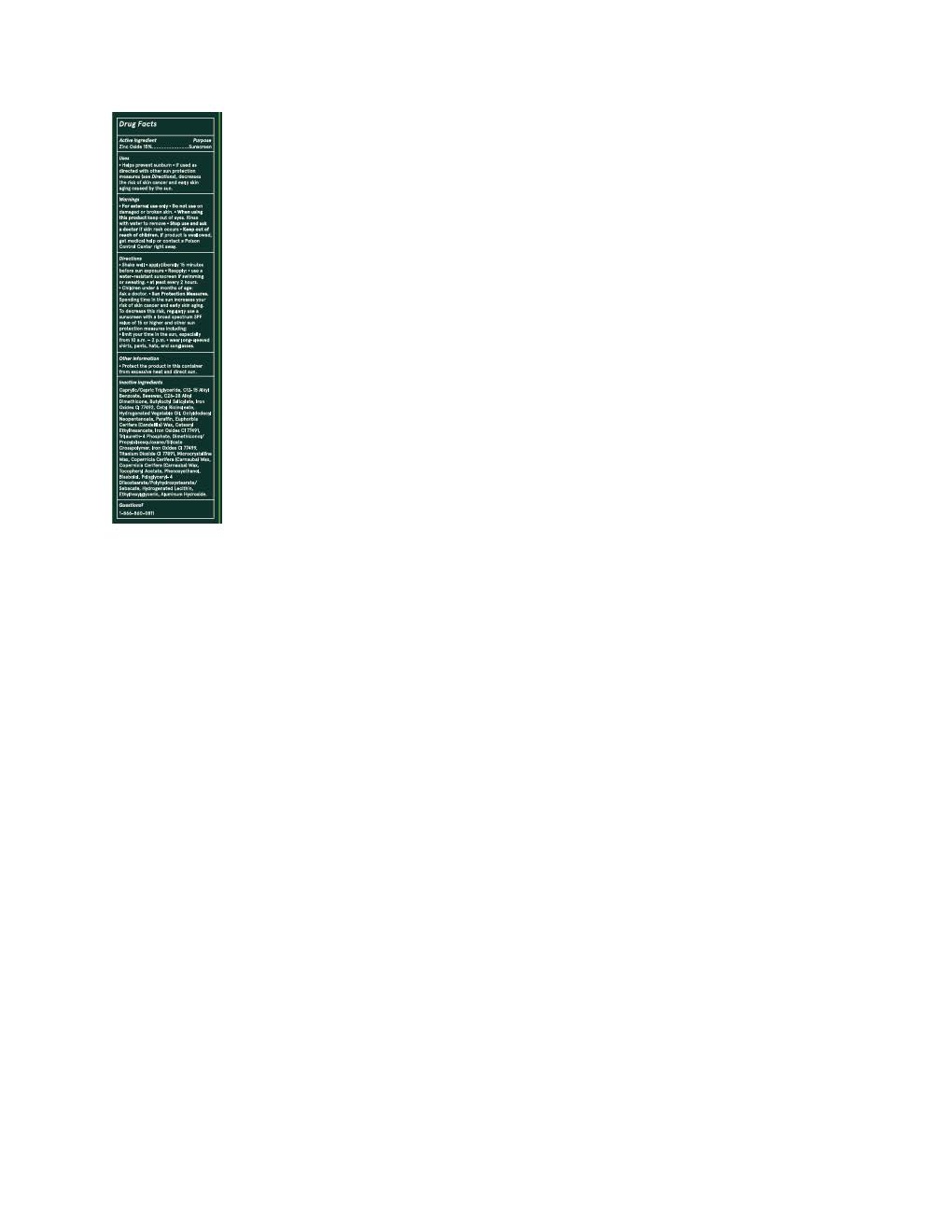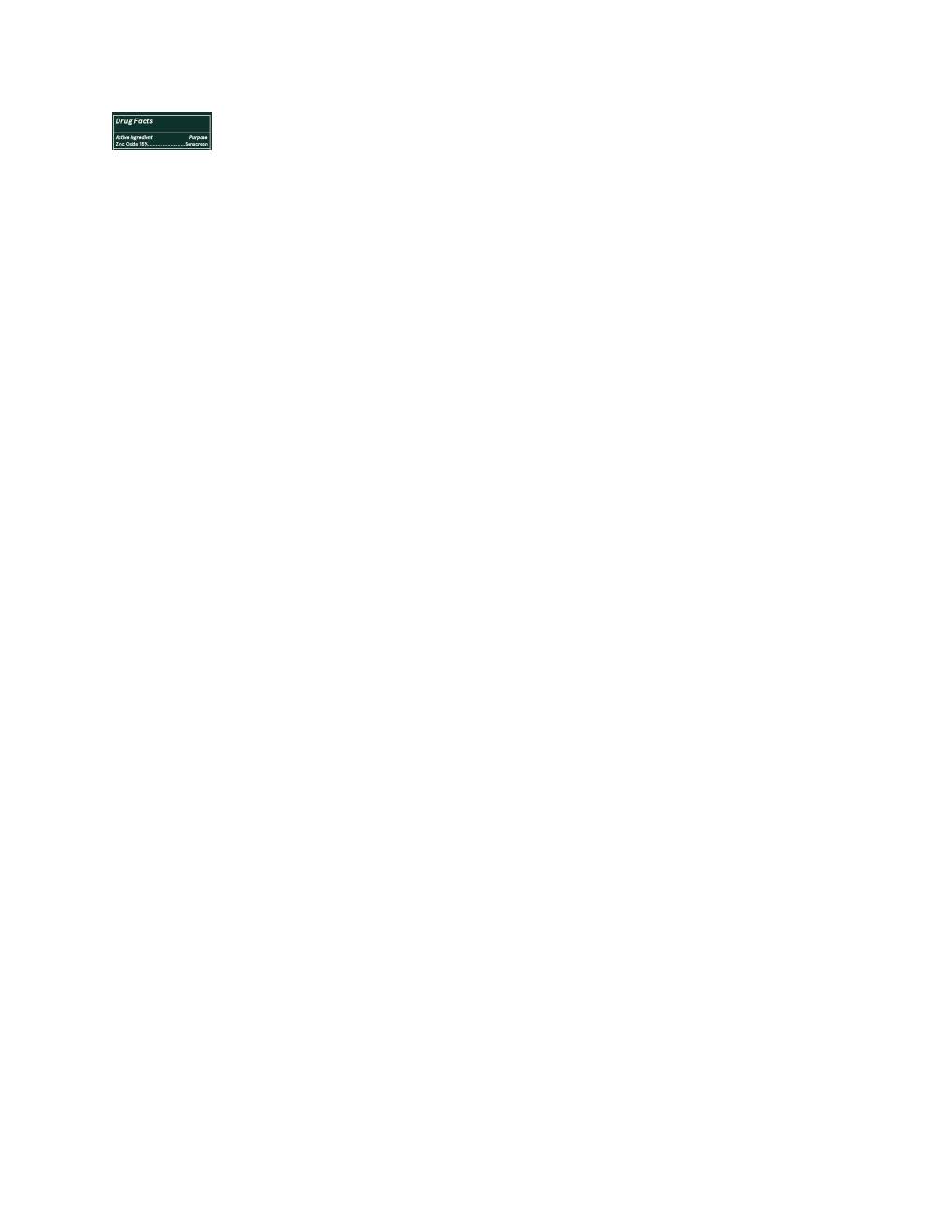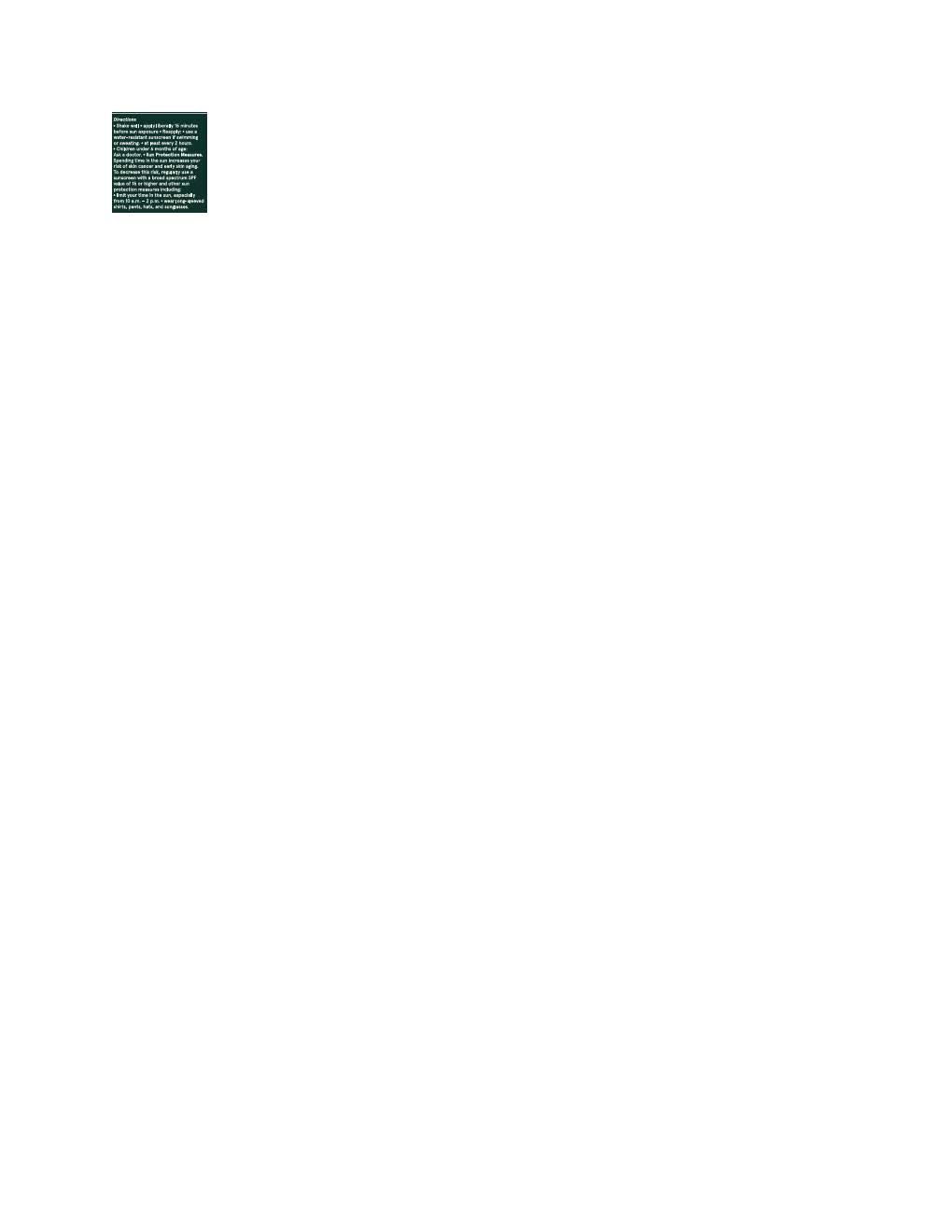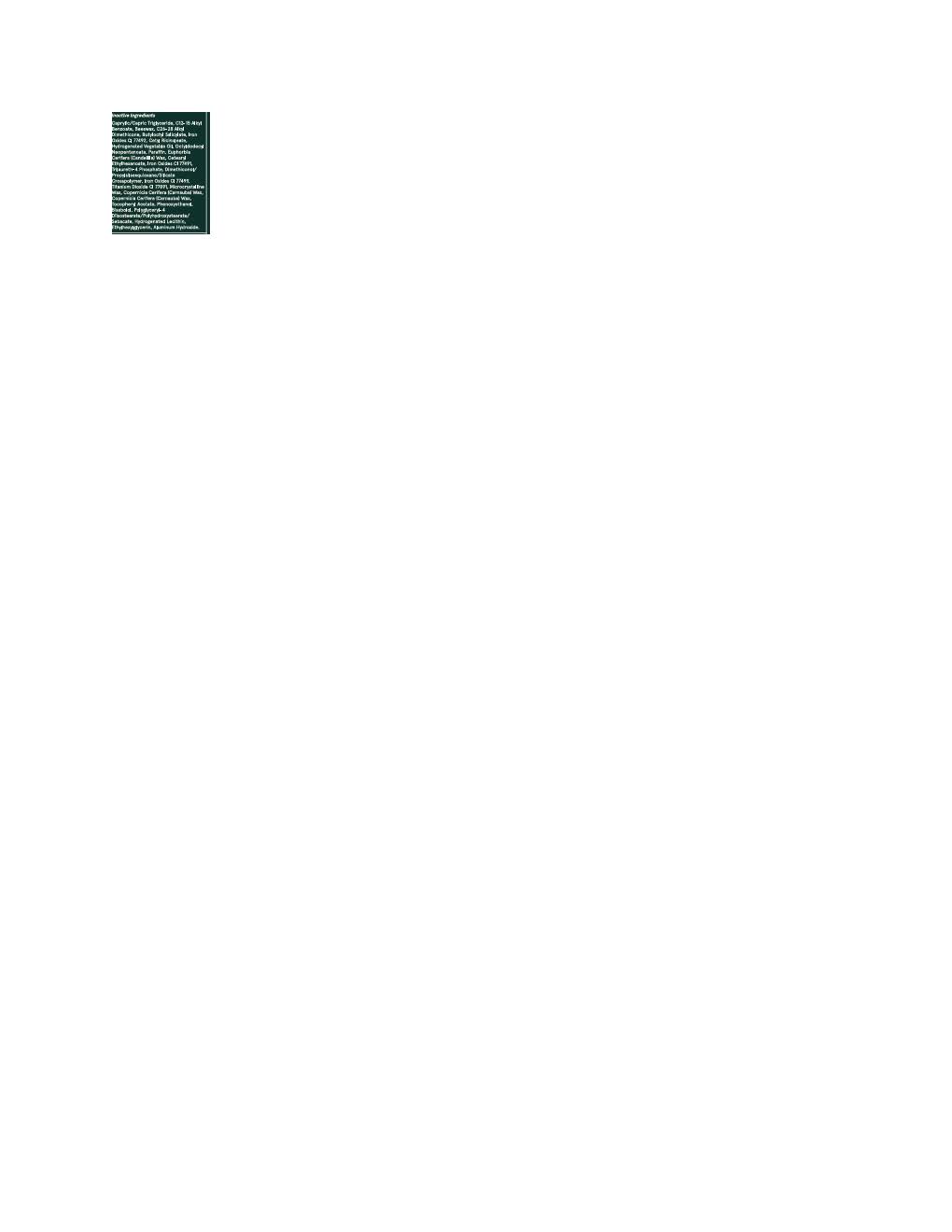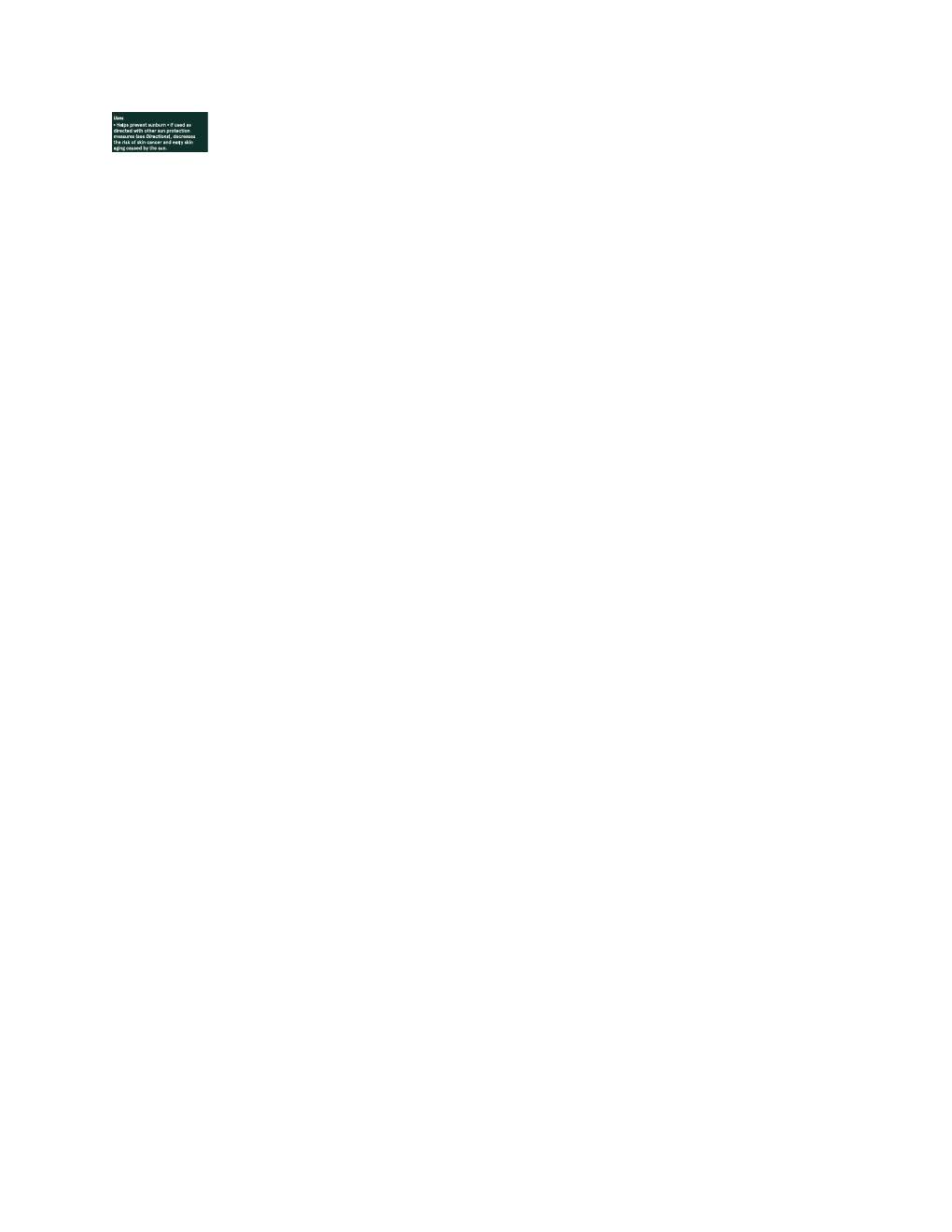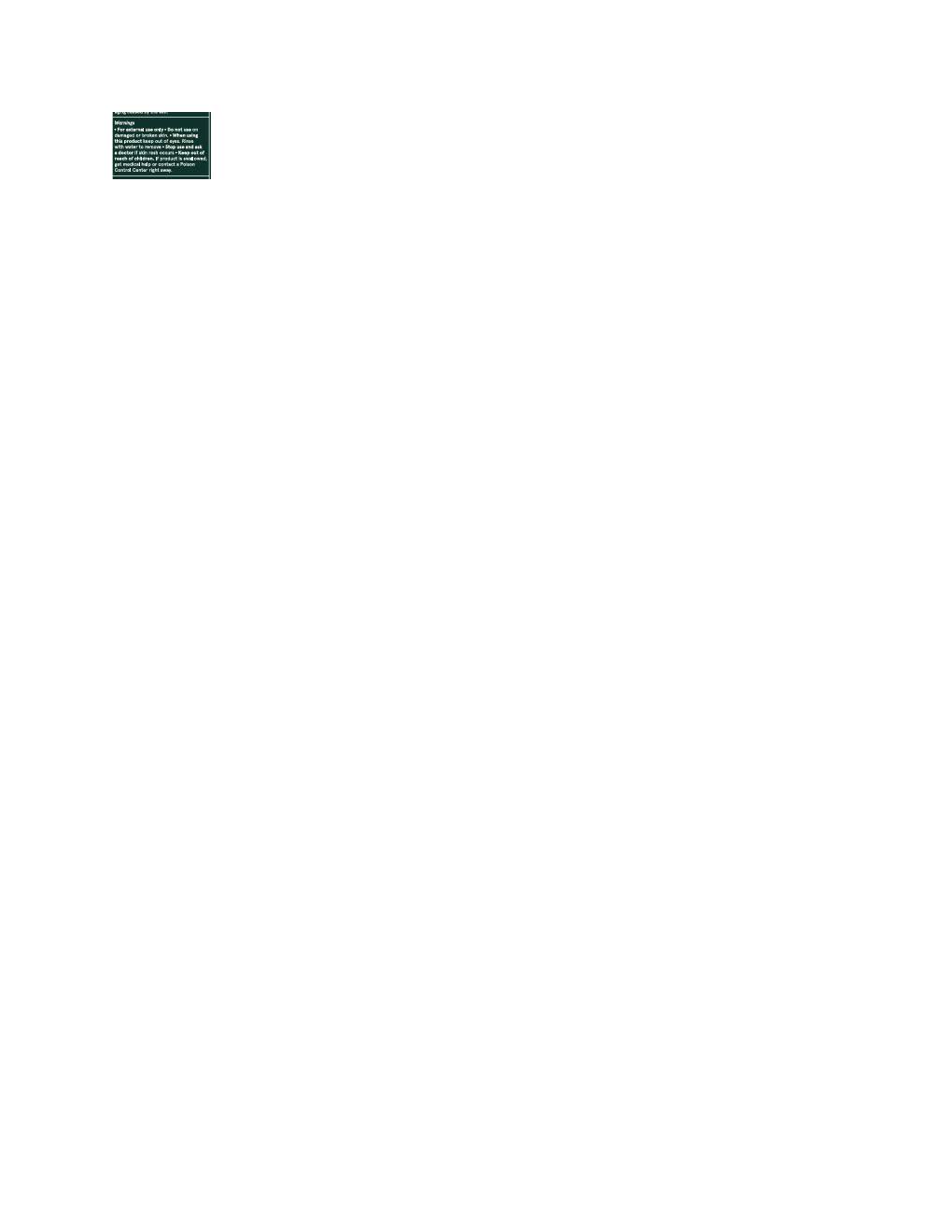 DRUG LABEL: Ciele Sculpt and Protect
NDC: 83103-1529 | Form: STICK
Manufacturer: Ciele LLC
Category: otc | Type: HUMAN OTC DRUG LABEL
Date: 20251015

ACTIVE INGREDIENTS: ZINC OXIDE 165 mg/1 g
INACTIVE INGREDIENTS: PARAFFIN; CETYL RICINOLEATE; CANDELILLA WAX; ETHYLHEXYLGLYCERIN; PHENOXYETHANOL; POLYGLYCERYL-4 DIISOSTEARATE/POLYHYDROXYSTEARATE/SEBACATE; ALKYL (C12-15) BENZOATE; TRILAURETH-4 PHOSPHATE; OCTYLDODECYL NEOPENTANOATE; CETEARYL ETHYLHEXANOATE; CARNAUBA WAX; DIMETHICONOL/PROPYLSILSESQUIOXANE/SILICATE CROSSPOLYMER (450000000 MW); LECITHIN, SOYBEAN; BUTYLOCTYL SALICYLATE; TITANIUM DIOXIDE; .ALPHA.-BISABOLOL, (+/-)-; MICROCRYSTALLINE WAX; FERRIC OXIDE RED; ALUMINUM HYDROXIDE; FERRIC OXIDE YELLOW

Ciele Sculpt and Protect